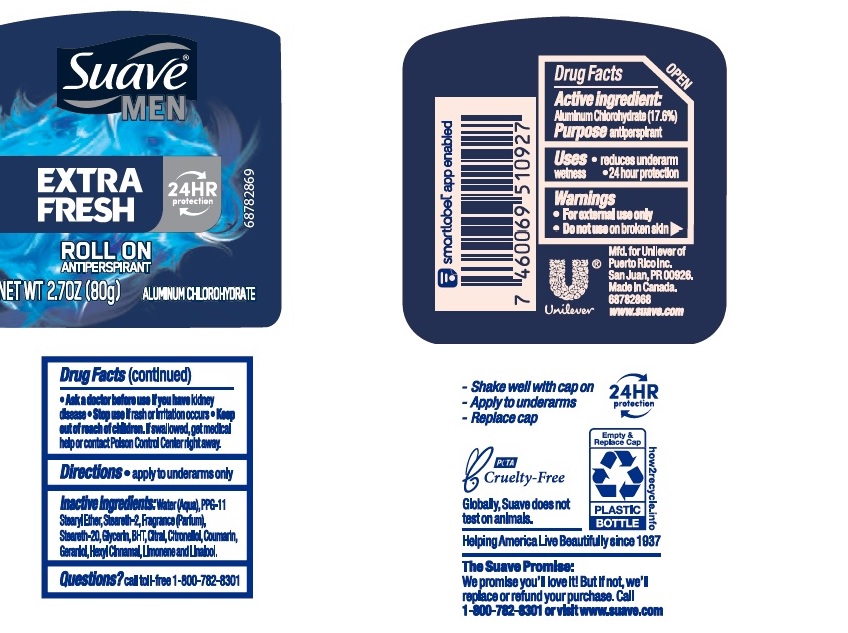 DRUG LABEL: Suave
NDC: 64942-2024 | Form: STICK
Manufacturer: Conopco Inc. d/b/a/ Unilever
Category: otc | Type: HUMAN OTC DRUG LABEL
Date: 20220414

ACTIVE INGREDIENTS: ALUMINUM CHLOROHYDRATE 17.6 g/100 g
INACTIVE INGREDIENTS: .ALPHA.-HEXYLCINNAMALDEHYDE; LINALOOL, (+/-)-; .BETA.-CITRONELLOL, (R)-; STEARETH-20; WATER; PPG-11 STEARYL ETHER; GLYCERIN; BUTYLATED HYDROXYTOLUENE; STEARETH-2; CITRAL; COUMARIN; GERANIOL; LIMONENE, (+)-

Suave Men Extra Fresh 24HR Roll On Antiperspirant

SUAVE MEN EXTRA FRESH 24HR ROLL ON ANTIPERSPIRANT - aluminum chlorohydrate stick

Suave Clinical Protection Coconut Kiss Antiperspirant

Drug Facts

Active ingredient

Aluminum Chlorohydrate (17.6)

Purpose

antiperspirant

Uses

• reduces underarm wetness
• 24 hour protection

Warnings

• For external use only
• Do not use on broken skin
• Ask a doctor before use if you have kidney disease
• Stop use if rash or irritation occurs

• Keep out of reach of children.

If swallowed, get medical help or contact a Poison Control Center right away.

Directions

• apply to underarms only

Inactive ingredients

Water (Aqua), PPG-11 Stearyl Ether, Steareth-2, Fragrance (Parfum), Steareth-20, Glycerin , BHT, Citral, Citonellol, Coumarin, Geraniol, Hexyl Cinnamal, Limonene, Linalool

Questions?

Call toll-free 1-800-782-8301